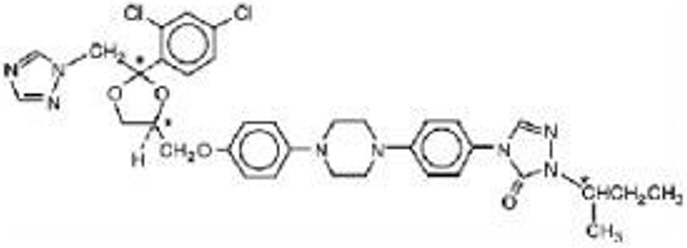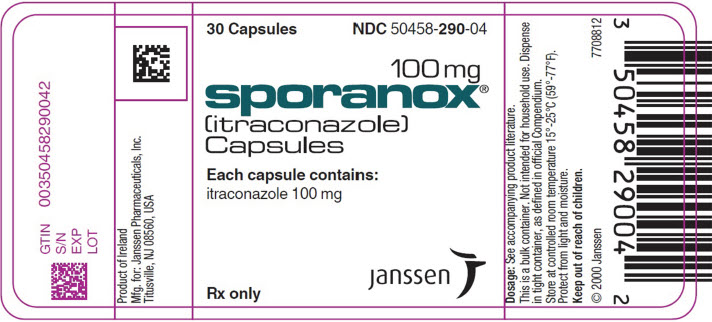 DRUG LABEL: SPORANOX
NDC: 50458-290 | Form: CAPSULE
Manufacturer: Janssen Pharmaceuticals, Inc.
Category: prescription | Type: HUMAN PRESCRIPTION DRUG LABEL
Date: 20260226

ACTIVE INGREDIENTS: ITRACONAZOLE 100 mg/1 1
INACTIVE INGREDIENTS: GELATIN, UNSPECIFIED; HYPROMELLOSE, UNSPECIFIED; POLYETHYLENE GLYCOL, UNSPECIFIED; STARCH, CORN; SUCROSE; TITANIUM DIOXIDE; FD&C BLUE NO. 1; FD&C BLUE NO. 2; D&C RED NO. 22; D&C RED NO. 28

SPORANOX®
(itraconazole)
Capsules

BOXED WARNING

Congestive Heart Failure, Cardiac Effects and Drug Interactions

Congestive Heart Failure and Cardiac Effects

- SPORANOX®(itraconazole) Capsules should not be administered for the treatment of onychomycosis in patients with evidence of ventricular dysfunction such as congestive heart failure (CHF) or a history of CHF. If signs or symptoms of congestive heart failure occur during administration of SPORANOX®Capsules, discontinue administration.
- When itraconazole was administered intravenously to dogs and healthy human volunteers, negative inotropic effects were seen. (See CONTRAINDICATIONS, WARNINGS, PRECAUTIONS: Drug Interactions, ADVERSE REACTIONS: Postmarketing Experience, and CLINICAL PHARMACOLOGY: Special Populationsfor more information.)

Drug Interactions

- Coadministration of a number of CYP3A4 substrates are contraindicated with SPORANOX®. Some examples of drugs that are contraindicated for coadministration with SPORANOX®Capsules are: methadone, disopyramide, dofetilide, dronedarone, quinidine, isavuconazole, ergot alkaloids (such as dihydroergotamine, ergometrine (ergonovine), ergotamine, methylergometrine (methylergonovine)), irinotecan, lurasidone, oral midazolam, pimozide, triazolam, felodipine, nisoldipine, ivabradine, ranolazine, eplerenone, cisapride, naloxegol, lomitapide, lovastatin, simvastatin, avanafil, ticagrelor, finerenone, voclosporin.
- Coadministration with colchicine, fesoterodine and solifenacin is contraindicated in subjects with varying degrees of renal or hepatic impairment.
- Coadministration with eliglustat is contraindicated in subjects that are poor or intermediate metabolizers of CYP2D6 and in subjects taking strong or moderate CYP2D6 inhibitors.
- Coadministration with venetoclax is contraindicated in patients with chronic lymphocytic leukemia (CLL)/small lymphocytic lymphoma (SLL) during the dose initiation and ramp-up phase of venetoclax. See PRECAUTIONS: Drug InteractionsSection for specific examples.
- Coadministration with itraconazole can cause elevated plasma concentrations of these drugs and may increase or prolong both the pharmacologic effects and/or adverse reactions to these drugs. For example, increased plasma concentrations of some of these drugs can lead to QT prolongation and ventricular tachyarrhythmias including occurrences of torsade de pointes, a potentially fatal arrhythmia. See CONTRAINDICATIONSand WARNINGSSections, and PRECAUTIONS: Drug InteractionsSection for specific examples.

DESCRIPTION

SPORANOX®is the brand name for itraconazole, an azole antifungal agent. Itraconazole is a 1:1:1:1 racemic mixture of four diastereomers (two enantiomeric pairs), each possessing three chiral centers. It may be represented by the following structural formula and nomenclature:

(±)-1-[(R*)- sec-butyl]-4-[ p-[4-[ p-[[(2 R*,4 S*)-2-(2,4-dichlorophenyl)-2-(1 H-1,2,4-triazol-1-ylmethyl)-1,3-dioxolan-4-yl]methoxy]phenyl]-1-piperazinyl]phenyl]-Δ^2-1,2,4-triazolin-5-one mixture with (±)-1-[(R*)- sec-butyl]-4-[ p-[4-[ p-[[(2 S*,4 R*)-2-(2,4-dichlorophenyl)-2-(1 H-1,2,4-triazol-1-ylmethyl)-1,3-dioxolan-4-yl]methoxy]phenyl]-1-piperazinyl]phenyl]-Δ^2-1,2,4-triazolin-5-one

or

(±)-1-[(RS)- sec-butyl]-4-[ p-[4-[ p-[[(2 R,4 S)-2-(2,4-dichlorophenyl)-2-(1 H-1,2,4-triazol-1-ylmethyl)-1,3-dioxolan-4-yl]methoxy]phenyl]-1-piperazinyl]phenyl]-Δ^2-1,2,4-triazolin-5-one

Itraconazole has a molecular formula of C35H38Cl2N8O4and a molecular weight of 705.64. It is a white to slightly yellowish powder. It is insoluble in water, very slightly soluble in alcohols, and freely soluble in dichloromethane. It has a pKa of 3.70 (based on extrapolation of values obtained from methanolic solutions) and a log (n-octanol/water) partition coefficient of 5.66 at pH 8.1.

SPORANOX®Capsules contain 100 mg of itraconazole coated on sugar spheres (composed of sucrose, maize starch, and purified water). Inactive ingredients are hard gelatin capsule, hypromellose, polyethylene glycol (PEG) 20,000, titanium dioxide, FD&C Blue No. 1, FD&C Blue No. 2, D&C Red No. 22 and D&C Red No. 28.

Meets USP Dissolution Test 2.

CLINICAL PHARMACOLOGY

Pharmacokinetics and Metabolism

General Pharmacokinetic Characteristics

Peak plasma concentrations of itraconazole are reached within 2 to 5 hours following oral administration. As a consequence of non-linear pharmacokinetics, itraconazole accumulates in plasma during multiple dosing. Steady-state concentrations are generally reached within about 15 days, with Cmaxvalues of 0.5 μg/mL, 1.1 μg/mL and 2.0 μg/mL after oral administration of 100 mg once daily, 200 mg once daily and 200 mg b.i.d., respectively. The terminal half-life of itraconazole generally ranges from 16 to 28 hours after single dose and increases to 34 to 42 hours with repeated dosing. Once treatment is stopped, itraconazole plasma concentrations decrease to an almost undetectable concentration within 7 to 14 days, depending on the dose and duration of treatment. Itraconazole mean total plasma clearance following intravenous administration is 278 mL/min. Itraconazole clearance decreases at higher doses due to saturable hepatic metabolism.

Absorption

Itraconazole is rapidly absorbed after oral administration. Peak plasma concentrations of itraconazole are reached within 2 to 5 hours following an oral capsule dose. The observed absolute oral bioavailability of itraconazole is about 55%.

The oral bioavailability of itraconazole is maximal when SPORANOX®(itraconazole) Capsules are taken immediately after a full meal. Absorption of itraconazole capsules is reduced in subjects with reduced gastric acidity, such as subjects taking medications known as gastric acid secretion suppressors (e.g., H2-receptor antagonists, proton pump inhibitors) or subjects with achlorhydria caused by certain diseases. (See PRECAUTIONS: Drug Interactions.) Absorption of itraconazole under fasted conditions in these subjects is increased when SPORANOX®Capsules are administered with an acidic beverage (such as a non-diet cola). When SPORANOX®Capsules were administered as a single 200-mg dose under fasted conditions with non-diet cola after ranitidine pretreatment, a H2-receptor antagonist, itraconazole absorption was comparable to that observed when SPORANOX®Capsules were administered alone. (See PRECAUTIONS: Drug Interactions.)

Itraconazole exposure is lower with the Capsule formulation than with the Oral Solution when the same dose of drug is given. (See WARNINGS.)

Distribution

Most of the itraconazole in plasma is bound to protein (99.8%), with albumin being the main binding component (99.6% for the hydroxy-metabolite). It has also a marked affinity for lipids. Only 0.2% of the itraconazole in plasma is present as free drug. Itraconazole is distributed in a large apparent volume in the body (>700 L), suggesting extensive distribution into tissues. Concentrations in lung, kidney, liver, bone, stomach, spleen and muscle were found to be two to three times higher than corresponding concentrations in plasma, and the uptake into keratinous tissues, skin in particular, up to four times higher. Concentrations in the cerebrospinal fluid are much lower than in plasma.

Metabolism

Itraconazole is extensively metabolized by the liver into a large number of metabolites. In vitrostudies have shown that CYP3A4 is the major enzyme involved in the metabolism of itraconazole. The main metabolite is hydroxy-itraconazole, which has in vitroantifungal activity comparable to itraconazole; trough plasma concentrations of this metabolite are about twice those of itraconazole.

Excretion

Itraconazole is excreted mainly as inactive metabolites in urine (35%) and in feces (54%) within one week of an oral solution dose. Renal excretion of itraconazole and the active metabolite hydroxy-itraconazole account for less than 1% of an intravenous dose. Based on an oral radiolabeled dose, fecal excretion of unchanged drug ranges from 3% to 18% of the dose.

As re-distribution of itraconazole from keratinous tissues appears to be negligible, elimination of itraconazole from these tissues is related to epidermal regeneration. Contrary to plasma, the concentration in skin persists for 2 to 4 weeks after discontinuation of a 4-week treatment and in nail keratin – where itraconazole can be detected as early as 1 week after start of treatment – for at least six months after the end of a 3-month treatment period.

Special Populations

Renal Impairment

Limited data are available on the use of oral itraconazole in patients with renal impairment. A pharmacokinetic study using a single 200 mg oral dose of itraconazole was conducted in three groups of patients with renal impairment (uremia: n=7; hemodialysis: n=7; and continuous ambulatory peritoneal dialysis: n=5). In uremic subjects with a mean creatinine clearance of 13 mL/min. × 1.73 m^2, the exposure, based on AUC, was slightly reduced compared with normal population parameters. This study did not demonstrate any significant effect of hemodialysis or continuous ambulatory peritoneal dialysis on the pharmacokinetics of itraconazole (Tmax, Cmax, and AUC0–8h). Plasma concentration-versus-time profiles showed wide intersubject variation in all three groups. After a single intravenous dose, the mean terminal half-lives of itraconazole in patients with mild (defined in this study as CrCl 50–79 mL/min), moderate (defined in this study as CrCl 20–49 mL/min), and severe renal impairment (defined in this study as CrCl <20 mL/min) were similar to that in healthy subjects (range of means 42–49 hours vs 48 hours in renally impaired patients and healthy subjects, respectively). Overall exposure to itraconazole, based on AUC, was decreased in patients with moderate and severe renal impairment by approximately 30% and 40%, respectively, as compared with subjects with normal renal function. Data are not available in renally impaired patients during long-term use of itraconazole. Dialysis has no effect on the half-life or clearance of itraconazole or hydroxy-itraconazole. (See PRECAUTIONSand DOSAGE AND ADMINISTRATION.)

Hepatic Impairment

Itraconazole is predominantly metabolized in the liver. A pharmacokinetic study was conducted in 6 healthy and 12 cirrhotic subjects who were administered a single 100 mg dose of itraconazole as capsule. A statistically significant reduction in mean Cmax(47%) and a twofold increase in the elimination half-life (37±17 hours vs. 16±5 hours) of itraconazole were noted in cirrhotic subjects compared with healthy subjects. However, overall exposure to itraconazole, based on AUC, was similar in cirrhotic patients and in healthy subjects. Data are not available in cirrhotic patients during long-term use of itraconazole. (See CONTRAINDICATIONS, PRECAUTIONS: Drug Interactions and DOSAGE AND ADMINISTRATION.)

Decreased Cardiac Contractility

When itraconazole was administered intravenously to anesthetized dogs, a dose-related negative inotropic effect was documented. In a healthy volunteer study of itraconazole intravenous infusion, transient, asymptomatic decreases in left ventricular ejection fraction were observed using gated SPECT imaging; these resolved before the next infusion, 12 hours later. If signs or symptoms of congestive heart failure appear during administration of SPORANOX® Capsules, SPORANOX® should be discontinued. (See BOXED WARNING, CONTRAINDICATIONS, WARNINGS, PRECAUTIONS: Drug Interactions and ADVERSE REACTIONS: Postmarketing Experience for more information.)

MICROBIOLOGY

Mechanism of Action

In vitrostudies have demonstrated that itraconazole inhibits the cytochrome P450-dependent synthesis of ergosterol, which is a vital component of fungal cell membranes.

Antimicrobial Activity

Itraconazole exhibits in vitroactivity against Blastomyces dermatitidis, Histoplasma capsulatum, Histoplasma duboisii, Aspergillus flavus, Aspergillus fumigatus, and Trichophytonspecies (See INDICATIONS AND USAGE: Description of Clinical Studies).

Susceptibility Testing Methods

For specific information regarding susceptibility test interpretive criteria and associated test methods and quality control standards recognized by FDA for this drug, please see: https://www.fda.gov/STIC.

Resistance

Isolates from several fungal species with decreased susceptibility to itraconazole have been isolated in vitroand from patients receiving prolonged therapy.

Itraconazole is not active against Zygomycetes (e.g., Rhizopus spp., Rhizomucor spp., Mucor spp. and Absidia spp.), Fusarium spp., Scedosporium spp. and Scopulariopsis spp.

Cross-Resistance

Several in vitrostudies have reported that some fungal clinical isolates with reduced susceptibility to one azole antifungal agent may also be less susceptible to other azole derivatives. The finding of cross-resistance is dependent on a number of factors, including the species evaluated, its clinical history, the particular azole compounds compared, and the type of susceptibility test that is performed.

Studies (both in vitroand in vivo) suggest that the activity of amphotericin B may be suppressed by prior azole antifungal therapy. As with other azoles, itraconazole inhibits the^14C-demethylation step in the synthesis of ergosterol, a cell wall component of fungi. Ergosterol is the active site for amphotericin B. In one study the antifungal activity of amphotericin B against Aspergillus fumigatusinfections in mice was inhibited by ketoconazole therapy. The clinical significance of test results obtained in this study is unknown.

INDICATIONS AND USAGE

SPORANOX®(itraconazole) Capsules are indicated for the treatment of the following fungal infections in immunocompromised and non-immunocompromisedpatients:

1. Blastomycosis, pulmonary and extrapulmonary
2. Histoplasmosis, including chronic cavitary pulmonary disease and disseminated, non-meningeal histoplasmosis, and
3. Aspergillosis, pulmonary and extrapulmonary, in patients who are intolerant of or who are refractory to amphotericin B therapy.

Specimens for fungal cultures and other relevant laboratory studies (wet mount, histopathology, serology) should be obtained before therapy to isolate and identify causative organisms. Therapy may be instituted before the results of the cultures and other laboratory studies are known; however, once these results become available, antiinfective therapy should be adjusted accordingly.

SPORANOX®Capsules are also indicated for the treatment of the following fungal infections in non-immunocompromisedpatients:

1. Onychomycosis of the toenail, with or without fingernail involvement, due to dermatophytes (tinea unguium), and
2. Onychomycosis of the fingernail due to dermatophytes (tinea unguium).

Prior to initiating treatment, appropriate nail specimens for laboratory testing (KOH preparation, fungal culture, or nail biopsy) should be obtained to confirm the diagnosis of onychomycosis.

(See CLINICAL PHARMACOLOGY: Special Populations, CONTRAINDICATIONS, WARNINGS, and ADVERSE REACTIONS: Postmarketing Experiencefor more information.)

Description of Clinical Studies

Blastomycosis

Analyses were conducted on data from two open-label, non-concurrently controlled studies (N=73 combined) in patients with normal or abnormal immune status. The median dose was 200 mg/day. A response for most signs and symptoms was observed within the first 2 weeks, and all signs and symptoms cleared between 3 and 6 months. Results of these two studies demonstrated substantial evidence of the effectiveness of itraconazole for the treatment of blastomycosis compared with the natural history of untreated cases.

Histoplasmosis

Analyses were conducted on data from two open-label, non-concurrently controlled studies (N=34 combined) in patients with normal or abnormal immune status (not including HIV-infected patients). The median dose was 200 mg/day. A response for most signs and symptoms was observed within the first 2 weeks, and all signs and symptoms cleared between 3 and 12 months. Results of these two studies demonstrated substantial evidence of the effectiveness of itraconazole for the treatment of histoplasmosis, compared with the natural history of untreated cases.

Histoplasmosis in HIV-infected patients

Data from a small number of HIV-infected patients suggested that the response rate of histoplasmosis in HIV-infected patients is similar to that of non-HIV-infected patients. The clinical course of histoplasmosis in HIV-infected patients is more severe and usually requires maintenance therapy to prevent relapse.

Aspergillosis

Analyses were conducted on data from an open-label, "single-patient-use" protocol designed to make itraconazole available in the U.S. for patients who either failed or were intolerant of amphotericin B therapy (N=190). The findings were corroborated by two smaller open-label studies (N=31 combined) in the same patient population. Most adult patients were treated with a daily dose of 200 to 400 mg, with a median duration of 3 months. Results of these studies demonstrated substantial evidence of effectiveness of itraconazole as a second-line therapy for the treatment of aspergillosis compared with the natural history of the disease in patients who either failed or were intolerant of amphotericin B therapy.

Onychomycosis of the toenail

Analyses were conducted on data from three double-blind, placebo-controlled studies (N=214 total; 110 given SPORANOX®Capsules) in which patients with onychomycosis of the toenails received 200 mg of SPORANOX®Capsules once daily for 12 consecutive weeks. Results of these studies demonstrated mycologic cure, defined as simultaneous occurrence of negative KOH plus negative culture, in 54% of patients. Thirty-five percent (35%) of patients were considered an overall success (mycologic cure plus clear or minimal nail involvement with significantly decreased signs) and 14% of patients demonstrated mycologic cure plus clinical cure (clearance of all signs, with or without residual nail deformity). The mean time to overall success was approximately 10 months. Twenty-one percent (21%) of the overall success group had a relapse (worsening of the global score or conversion of KOH or culture from negative to positive).

Onychomycosis of the fingernail

Analyses were conducted on data from a double-blind, placebo-controlled study (N=73 total; 37 given SPORANOX®Capsules) in which patients with onychomycosis of the fingernails received a 1-week course (pulse) of 200 mg of SPORANOX®Capsules b.i.d., followed by a 3-week period without SPORANOX®, which was followed by a second 1-week pulse of 200 mg of SPORANOX®Capsules b.i.d. Results demonstrated mycologic cure in 61% of patients. Fifty-six percent (56%) of patients were considered an overall success and 47% of patients demonstrated mycologic cure plus clinical cure. The mean time to overall success was approximately 5 months. None of the patients who achieved overall success relapsed.

CONTRAINDICATIONS

Congestive Heart Failure

SPORANOX®(itraconazole) Capsules should not be administered for the treatment of onychomycosis in patients with evidence of ventricular dysfunction such as congestive heart failure (CHF) or a history of CHF. (See BOXED WARNING, WARNINGS, PRECAUTIONS: Drug Interactions-Calcium Channel Blockers, ADVERSE REACTIONS: Postmarketing Experience, and CLINICAL PHARMACOLOGY: Special Populations.)

Drug Interactions

Coadministration of a number of CYP3A4 substrates are contraindicated with SPORANOX®. Some examples of drugs for which plasma concentrations increase are: methadone, disopyramide, dofetilide, dronedarone, quinidine, isavuconazole, ergot alkaloids (such as dihydroergotamine, ergometrine (ergonovine), ergotamine, methylergometrine (methylergonovine)), irinotecan, lurasidone, oral midazolam, pimozide, triazolam, felodipine, nisoldipine, ivabradine, ranolazine, eplerenone, cisapride, naloxegol, lomitapide, lovastatin, simvastatin, avanafil, ticagrelor, finerenone, voclosporin. In addition, coadministration with colchicine, fesoterodine and solifenacin is contraindicated in subjects with varying degrees of renal or hepatic impairment, and coadministration with eliglustat is contraindicated in subjects that are poor or intermediate metabolizers of CYP2D6 and in subjects taking strong or moderate CYP2D6 inhibitors. (See PRECAUTIONS: Drug Interactions Section for specific examples.) This increase in drug concentrations caused by coadministration with itraconazole may increase or prolong both the pharmacologic effects and/or adverse reactions to these drugs. For example, increased plasma concentrations of some of these drugs can lead to QT prolongation and ventricular tachyarrhythmias including occurrences of torsade de pointes, a potentially fatal arrhythmia. Some specific examples are listed in PRECAUTIONS: Drug Interactions.

Coadministration with venetoclax is contraindicated in patients with CLL/SLL during the dose initiation and ramp-up phase of venetoclax due to the potential for an increased risk of tumor lysis syndrome.

SPORANOX® should not be administered for the treatment of onychomycosis to pregnant patients or to women contemplating pregnancy.

SPORANOX® is contraindicated for patients who have shown hypersensitivity to itraconazole. There is limited information regarding cross-hypersensitivity between itraconazole and other azole antifungal agents. Caution should be used when prescribing SPORANOX® to patients with hypersensitivity to other azoles.

WARNINGS

Hepatic Effects

SPORANOX® has been associated with rare cases of serious hepatotoxicity, including liver failure and death. Some of these cases had neither pre-existing liver disease nor a serious underlying medical condition, and some of these cases developed within the first week of treatment. If clinical signs or symptoms develop that are consistent with liver disease, treatment should be discontinued and liver function testing performed. Continued SPORANOX® use or reinstitution of treatment with SPORANOX® is strongly discouraged unless there is a serious or life-threatening situation where the expected benefit exceeds the risk. (See PRECAUTIONS: Information for Patients and ADVERSE REACTIONS.)

Cardiac Dysrhythmias

Life-threatening cardiac dysrhythmias and/or sudden death have occurred in patients using drugs such as cisapride, pimozide, methadone, or quinidine concomitantly with SPORANOX®and/or other CYP3A4 inhibitors. Concomitant administration of these drugs with SPORANOX®is contraindicated. (See BOXED WARNING, CONTRAINDICATIONS, and PRECAUTIONS: Drug Interactions.)

Cardiac Disease

SPORANOX® Capsules should not be administered for the treatment of onychomycosis in patients with evidence of ventricular dysfunction such as congestive heart failure (CHF) or a history of CHF. SPORANOX® Capsules should not be used for other indications in patients with evidence of ventricular dysfunction unless the benefit clearly outweighs the risk.

For patients with risk factors for congestive heart failure, physicians should carefully review the risks and benefits of SPORANOX® therapy. These risk factors include cardiac disease such as ischemic and valvular disease; significant pulmonary disease such as chronic obstructive pulmonary disease; and renal failure and other edematous disorders. Such patients should be informed of the signs and symptoms of CHF, should be treated with caution, and should be monitored for signs and symptoms of CHF during treatment. If signs or symptoms of CHF appear during administration of SPORANOX® Capsules, discontinue administration.

Itraconazole has been shown to have a negative inotropic effect. When itraconazole was administered intravenously to anesthetized dogs, a dose-related negative inotropic effect was documented. In a healthy volunteer study of itraconazole intravenous infusion, transient, asymptomatic decreases in left ventricular ejection fraction were observed using gated SPECT imaging; these resolved before the next infusion, 12 hours later.

SPORANOX® has been associated with reports of congestive heart failure. In postmarketing experience, heart failure was more frequently reported in patients receiving a total daily dose of 400 mg although there were also cases reported among those receiving lower total daily doses.

Calcium channel blockers can have negative inotropic effects which may be additive to those of itraconazole. In addition, itraconazole can inhibit the metabolism of calcium channel blockers. Therefore, caution should be used when co-administering itraconazole and calcium channel blockers due to an increased risk of CHF. Concomitant administration of SPORANOX®and felodipine or nisoldipine is contraindicated.

Cases of CHF, peripheral edema, and pulmonary edema have been reported in the postmarketing period among patients being treated for onychomycosis and/or systemic fungal infections. (See CLINICAL PHARMACOLOGY: Special Populations, CONTRAINDICATIONS, PRECAUTIONS: Drug Interactions, and ADVERSE REACTIONS: Postmarketing Experience for more information.)

Pseudoaldosteronism

Pseudoaldosteronism, manifested by the onset of hypertension or worsening of hypertension, and abnormal laboratory findings (hypokalemia, low serum renin and aldosterone, and elevated 11-deoxycortisol), has been reported with itraconazole use in the postmarketing setting. Monitor blood pressure and potassium levels and manage as necessary. Management of pseudoaldosteronism may include discontinuation of SPORANOX®, substitution with an appropriate antifungal drug that is not associated with pseudoaldosteronism, or use of aldosterone receptor antagonists.

Interaction Potential

SPORANOX®has a potential for clinically important drug interactions. Coadministration of specific drugs with itraconazole may result in changes in efficacy of itraconazole and/or the coadministered drug, life-threatening effects and/or sudden death. Drugs that are contraindicated, not recommended or recommended for use with caution in combination with itraconazole are listed in PRECAUTIONS: Drug Interactions.

Interchangeability

SPORANOX®(itraconazole) Capsules and SPORANOX®Oral Solution should not be used interchangeably. This is because drug exposure is greater with the Oral Solution than with the Capsules when the same dose of drug is given. In addition, the topical effects of mucosal exposure may be different between the two formulations. Only the Oral Solution has been demonstrated effective for oral and/or esophageal candidiasis.

PRECAUTIONS

General

SPORANOX®(itraconazole) Capsules should be administered after a full meal. (See CLINICAL PHARMACOLOGY: Pharmacokinetics and Metabolism).

Under fasted conditions, itraconazole absorption was decreased in the presence of decreased gastric acidity. The absorption of itraconazole may be decreased with the concomitant administration of antacids or gastric acid secretion suppressors. Studies conducted under fasted conditions demonstrated that administration with 8 ounces of a non-diet cola beverage resulted in increased absorption of itraconazole in AIDS patients with relative or absolute achlorhydria. This increase relative to the effects of a full meal is unknown. (See CLINICAL PHARMACOLOGY: Pharmacokinetics and Metabolism).

Hepatotoxicity

Rare cases of serious hepatotoxicity have been observed with SPORANOX®treatment, including some cases within the first week. It is recommended that liver function monitoring be considered in all patients receiving SPORANOX®. Treatment should be stopped immediately and liver function testing should be conducted in patients who develop signs and symptoms suggestive of liver dysfunction.

Neuropathy

If neuropathy occurs that may be attributable to SPORANOX®Capsules, the treatment should be discontinued.

Immunocompromised Patients

In some immunocompromised patients (e.g., neutropenic, AIDS or organ transplant patients), the oral bioavailability of SPORANOX®capsules may be decreased. Therefore, the dose should be adjusted based on the clinical response in these patients.

Cystic Fibrosis

If a cystic fibrosis patient does not respond to SPORANOX®Capsules, consideration should be given to switching to alternative therapy. For more information concerning the use of itraconazole in cystic fibrosis patients see the prescribing information for SPORANOX®Oral Solution.

Hearing Loss

Transient or permanent hearing loss has been reported in patients receiving treatment with itraconazole. Several of these reports included concurrent administration of quinidine which is contraindicated (See BOXED WARNING: Drug Interactions, CONTRAINDICATIONS: Drug Interactionsand PRECAUTIONS: Drug Interactions). The hearing loss usually resolves when treatment is stopped, but can persist in some patients.

Information for Patients

- The topical effects of mucosal exposure may be different between the SPORANOX®Capsules and Oral Solution. Only the Oral Solution has been demonstrated effective for oral and/or esophageal candidiasis. SPORANOX®Capsules should not be used interchangeably with SPORANOX®Oral Solution.
- Instruct patients to take SPORANOX®Capsules with a full meal. SPORANOX®Capsules must be swallowed whole.
- Instruct patients about the signs and symptoms of congestive heart failure, and if these signs or symptoms occur during SPORANOX®administration, they should discontinue SPORANOX®and contact their healthcare provider immediately.
- Instruct patients to stop SPORANOX®treatment immediately and contact their healthcare provider if any signs and symptoms suggestive of liver dysfunction develop. Such signs and symptoms may include unusual fatigue, anorexia, nausea and/or vomiting, jaundice, dark urine, or pale stools.
- Instruct patients to contact their physician before taking any concomitant medications with itraconazole to ensure there are no potential drug interactions.
- Instruct patients that hearing loss can occur with the use of itraconazole. The hearing loss usually resolves when treatment is stopped, but can persist in some patients. Advise patients to discontinue therapy and inform their physicians if any hearing loss symptoms occur.
- Instruct patients that dizziness or blurred/double vision can sometimes occur with itraconazole. Advise patients that if they experience these events, they should not drive or use machines.

Drug Interactions

Effect of SPORANOX®on Other Drugs

Itraconazole and its major metabolite, hydroxy-itraconazole, are potent CYP3A4 inhibitors. Itraconazole is an inhibitor of the drug transporters P-glycoprotein and breast cancer resistance protein (BCRP). Consequently, SPORANOX® has the potential to interact with many concomitant drugs resulting in either increased or sometimes decreased concentrations of the concomitant drugs. Increased concentrations may increase the risk of adverse reactions associated with the concomitant drug which can be severe or life-threatening in some cases (e.g., QT prolongation, torsade de pointes, respiratory depression, hepatic adverse reactions, hypersensitivity reactions, myelosuppression, hypotension, seizures, angioedema, atrial fibrillation, bradycardia, priapism). Reduced concentrations of concomitant drugs may reduce their efficacy. Table 1 lists examples of drugs that may have their concentrations affected by itraconazole, but it is not a comprehensive list.

Refer to the approved product labeling to become familiar with the interaction pathways, risk potential, and specific actions to be taken with regards to each concomitant drug prior to initiating therapy with SPORANOX®.

Although many of the clinical drug interactions in Table 1 are based on information with a similar azole antifungal, ketoconazole, these interactions are expected to occur with SPORANOX®.

Table 1: Drug Interactions with SPORANOX® that Affect Concomitant Drug Concentrations
Examples of Concomitant Drugs Within Class |  | Prevention or Management
Drug Interactions with SPORANOX® that Increase Concomitant Drug Concentrations and May Increase Risk of Adverse Reactions Associated with the Concomitant Drug
Alpha Blockers
Alfuzosin Silodosin Tamsulosin |  | Not recommended during and 2 weeks after SPORANOX®treatment.
Analgesics
Methadone |  | Contraindicated during and 2 weeks after SPORANOX® treatment.
Fentanyl |  | Not recommended during and 2 weeks after SPORANOX® treatment.
Alfentanil Buprenorphine (IV and sublingual) Oxycodone [Based on clinical drug interaction information with itraconazole.] Sufentanil |  | Monitor for adverse reactions. Concomitant drug dose reduction may be necessary.
Antiarrhythmics
Disopyramide Dofetilide Dronedarone Quinidine |  | Contraindicated during and 2 weeks after SPORANOX® treatment.
Digoxin |  | Monitor for adverse reactions. Concomitant drug dose reduction may be necessary.
Antibacterials
Bedaquiline [Based on 400 mg bedaquiline once daily for 2 weeks.] |  | Concomitant SPORANOX® not recommended for more than 2 weeks at any time during bedaquiline treatment.
Rifabutin |  | Not recommended 2 weeks before, during, and 2 weeks after SPORANOX® treatment. See also Table 2.
Clarithromycin |  | Monitor for adverse reactions. Concomitant drug dose reduction may be necessary. See also Table 2.
Trimetrexate |  | Monitor for adverse reactions. Concomitant drug dose reduction may be necessary.
Anticoagulants and Antiplatelets
Ticagrelor |  | Contraindicated during and 2 weeks after SPORANOX® treatment.
Apixaban Rivaroxaban Vorapaxar |  | Not recommended during and 2 weeks after SPORANOX® treatment.
Cilostazol Dabigatran Warfarin |  | Monitor for adverse reactions. Concomitant drug dose reduction may be necessary.
Anticonvulsants
Carbamazepine |  | Not recommended 2 weeks before, during, and 2 weeks after SPORANOX®treatment. See also Table 2.
Antidiabetic Drugs
Repaglinide Saxagliptin |  | Monitor for adverse reactions. Concomitant drug dose reduction may be necessary.
Antihelminthics, Antifungals and Antiprotozoals
Isavuconazonium |  | Contraindicated during and 2 weeks after SPORANOX® treatment.
Praziquantel |  | Monitor for adverse reactions. Concomitant drug dose reduction may be necessary.
Artemether-lumefantrine Quinine |  | Monitor for adverse reactions.
Antimigraine Drugs
Ergot alkaloids (e.g., dihydroergotamine, ergotamine) |  | Contraindicated during and 2 weeks after SPORANOX® treatment.
Eletriptan |  | Monitor for adverse reactions. Concomitant drug dose reduction may be necessary.
Antineoplastics
Irinotecan |  | Contraindicated during and 2 weeks after SPORANOX® treatment.
Venetoclax |  | Contraindicated during the dose initiation and ramp-up phase in patients with CLL/SLL. Refer to the venetoclax prescribing information for dosing and safety monitoring instructions.
Mobocertinib |  | Avoid use during and 2 weeks after SPORANOX® treatment.
Axitinib Bosutinib Cabazitaxel Cabozantinib Ceritinib Cobimetinib Crizotinib Dabrafenib Dasatinib Docetaxel | Ibrutinib Lapatinib Nilotinib Olaparib Pazopanib Sunitinib Trabectedin Trastuzumab-emtansine Vinca alkaloids | Avoid use during and 2 weeks after SPORANOX® treatment.
Entrectinib Pemigatinib Talazoparib |  | Refer to the entrectinib, pemigatinib and talazoparib prescribing information for dosing instructions if concomitant use cannot be avoided.
Glasdegib |  | Refer to the glasdegib prescribing information for safety monitoring if concomitant use cannot be avoided.
Bortezomib Brentuximab-vedotin Busulfan Erlotinib Gefitinib Idelalisib Imatinib Ixabepilone | Nintedanib Panobinostat Ponatinib Ruxolitinib Sonidegib Tretinoin (oral) Vandetanib | Monitor for adverse reactions. Concomitant drug dose reduction may be necessary. For idelalisib, see also Table 2.
Antipsychotics, Anxiolytics and Hypnotics
Alprazolam Aripiprazole Buspirone Cariprazine Diazepam Haloperidol | Midazolam (IV) Quetiapine Ramelteon Risperidone Suvorexant | Monitor for adverse reactions. Concomitant drug dose reduction may be necessary.
Zopiclone |  | Monitor for adverse reactions. Concomitant drug dose reduction may be necessary.
Lurasidone Midazolam (oral) Pimozide Triazolam |  | Contraindicated during and 2 weeks after SPORANOX® treatment.
Antivirals
Daclatasvir Indinavir Maraviroc |  | Monitor for adverse reactions. Concomitant drug dose reduction may be necessary. For indinavir, see also Table 2.
Cobicistat Elvitegravir (ritonavir-boosted) Ombitasvir/Paritaprevir/Ritonavir with or without Dasabuvir Ritonavir Saquinavir (unboosted) |  | Monitor for adverse reactions. See also Table 2.
Elbasvir/grazoprevir |  | Not recommended during and 2 weeks after SPORANOX® treatment.
Glecaprevir/pibrentasvir |  | Monitor for adverse reactions.
Tenofovir disoproxil fumarate |  | Monitor for adverse reactions.
Beta Blockers
Nadolol |  | Monitor for adverse reactions. Concomitant drug dose reduction may be necessary.
Calcium Channel Blockers
Felodipine Nisoldipine |  | Contraindicated during and 2 weeks after SPORANOX® treatment.
Diltiazem Other dihydropyridines Verapamil |  | Monitor for adverse reactions. Concomitant drug dose reduction may be necessary. For diltiazem, see also Table 2.
Cardiovascular Drugs, Miscellaneous
Ivabradine Ranolazine |  | Contraindicated during and 2 weeks after SPORANOX® treatment.
Aliskiren Riociguat Sildenafil (for pulmonary hypertension) Tadalafil (for pulmonary hypertension) |  | Not recommended during and 2 weeks after SPORANOX® treatment. For sildenafil and tadalafil, see also Urologic Drugs below.
Bosentan Guanfacine |  | Monitor for adverse reactions. Concomitant drug dose reduction may be necessary.
Contraceptives [CYP3A4 inhibitors (including itraconazole) may increase systemic contraceptive hormone concentrations.]
Dienogest Ulipristal |  | Monitor for adverse reactions.
Diuretics
Eplerenone Finerenone |  | Contraindicated during and 2 weeks after SPORANOX®treatment.
Gastrointestinal Drugs
Cisapride Naloxegol |  | Contraindicated during and 2 weeks after SPORANOX®treatment.
Aprepitant Loperamide |  | Monitor for adverse reactions. Concomitant drug dose reduction may be necessary.
Netupitant |  | Monitor for adverse reactions.
Immunosuppressants
Voclosporin |  | Contraindicated during and for 2 weeks after SPORANOX®treatment.
Everolimus Sirolimus Temsirolimus (IV) |  | Not recommended during and 2 weeks after SPORANOX®treatment.
Budesonide (inhalation) Budesonide (non-inhalation) Ciclesonide (inhalation) Cyclosporine (IV) Cyclosporine (non-IV) Dexamethasone | Fluticasone (inhalation) Fluticasone (nasal) Methylprednisolone Tacrolimus (IV) Tacrolimus (oral) | Monitor for adverse reactions. Concomitant drug dose reduction may be necessary.
Lipid-Lowering Drugs
Lomitapide Lovastatin Simvastatin |  | Contraindicated during and 2 weeks after SPORANOX®treatment.
Atorvastatin |  | Monitor for drug adverse reactions. Concomitant drug dose reduction may be necessary.
Respiratory Drugs
Salmeterol |  | Not recommended during and 2 weeks after SPORANOX®treatment.
SSRIs, Tricyclics and Related Antidepressants
Venlafaxine |  | Monitor for adverse reactions. Concomitant drug dose reduction may be necessary.
Urologic Drugs
Avanafil |  | Contraindicated during and 2 weeks after SPORANOX®treatment.
Fesoterodine |  | Patients with moderate to severe renal or hepatic impairment: Contraindicated during and 2 weeks after SPORANOX®treatment. Other patients: Monitor for adverse reactions. Concomitant drug dose reduction may be necessary.
Solifenacin |  | Patients with severe renal or moderate to severe hepatic impairment: Contraindicated during and 2 weeks after SPORANOX®treatment. Other patients: Monitor for adverse reactions. Concomitant drug dose reduction may be necessary.
Darifenacin Vardenafil |  | Not recommended during and 2 weeks after SPORANOX®treatment.
Dutasteride Oxybutynin Sildenafil (for erectile dysfunction) Tadalafil (for erectile dysfunction and benign prostatic hyperplasia) Tolterodine |  | Monitor for adverse reactions. Concomitant drug dose reduction may be necessary. For sildenafil and tadalafil, see also Cardiovascular Drugs above.
Miscellaneous Drugs and Other Substances
Colchicine |  | Patients with renal or hepatic impairment: Contraindicated during and 2 weeks after SPORANOX® treatment. Other patients: Not recommended during and 2 weeks after SPORANOX® treatment.
Eliglustat |  | CYP2D6 EMs [EMs: extensive metabolizers; IMs: intermediate metabolizers, PMs: poor metabolizers] taking a strong or moderate CYP2D6 inhibitor, CYP2D6 IMs , or CYP2D6 PMs : Contraindicated during and 2 weeks after SPORANOX®treatment. CYP2D6 EMs not taking a strong or moderate CYP2D6 inhibitor : Monitor for adverse reactions. Eliglustat dose reduction may be necessary.
Lumacaftor/Ivacaftor |  | Not recommended 2 weeks before, during, and 2 weeks after SPORANOX®treatment.
Alitretinoin (oral) Cabergoline Cannabinoids Cinacalcet Galantamine Ivacaftor |  | Monitor for adverse reactions. Concomitant drug dose reduction may be necessary.
Valbenazine |  | Concomitant drug dose reduction is necessary. Refer to the valbenazine prescribing information for dosing instructions.
Vasopressin Receptor Antagonists
Conivaptan Tolvaptan |  | Not recommended during and 2 weeks after SPORANOX®treatment.
Drug Interactions with SPORANOX®that Decrease Concomitant Drug Concentrations and May Reduce Efficacy of the Concomitant Drug
Antineoplastics
Regorafenib |  | Not recommended during and 2 weeks after SPORANOX®treatment.
Gastrointestinal Drugs
Saccharomyces boulardii |  | Not recommended during and 2 weeks after SPORANOX®treatment.
Nonsteroidal Anti-Inflammatory Drugs
Meloxicam |  | Concomitant drug dose increase may be necessary.

Effect of Other Drugs on SPORANOX®

Itraconazole is mainly metabolized through CYP3A4. Other substances that either share this metabolic pathway or modify CYP3A4 activity may influence the pharmacokinetics of itraconazole. Some concomitant drugs have the potential to interact with SPORANOX®resulting in either increased or sometimes decreased concentrations of SPORANOX®. Increased concentrations may increase the risk of adverse reactions associated with SPORANOX®. Decreased concentrations may reduce SPORANOX®efficacy.

Table 2 lists examples of drugs that may affect itraconazole concentrations, but is not a comprehensive list. Refer to the approved product labeling to become familiar with the interaction pathways, risk potential and specific actions to be taken with regards to each concomitant drug prior to initiating therapy with SPORANOX®.

Although many of the clinical drug interactions in Table 2 are based on information with a similar azole antifungal, ketoconazole, these interactions are expected to occur with SPORANOX®.

Table 2: Drug Interactions with Other Drugs that Affect SPORANOX®Concentrations
Examples of Concomitant Drugs Within Class | Prevention or Management
Drug Interactions with Other Drugs that Increase SPORANOX® Concentrations and May Increase Risk of Adverse Reactions Associated with SPORANOX®
Antibacterials
Ciprofloxacin [Based on clinical drug interaction information with itraconazole.] Erythromycin Clarithromycin | Monitor for adverse reactions. SPORANOX®dose reduction may be necessary.
Antineoplastics
Idelalisib | Monitor for adverse reactions. SPORANOX®dose reduction may be necessary. See also Table 1.
Antivirals
Cobicistat Darunavir (ritonavir-boosted) Elvitegravir (ritonavir-boosted) Fosamprenavir (ritonavir-boosted) Indinavir Ombitasvir/ Paritaprevir/ Ritonavir with or without Dasabuvir Ritonavir Saquinavir | Monitor for adverse reactions. SPORANOX®dose reduction may be necessary. For, cobicistat, elvitegravir, indinavir, ombitasvir/ paritaprevir/ ritonavir with or without dasabuvir, ritonavir, and saquinavir, see also Table 1.
Calcium Channel Blockers
Diltiazem | Monitor for adverse reactions. SPORANOX®dose reduction may be necessary. See also Table 1.
Drug Interactions with Other Drugs that Decrease SPORANOX®Concentrations and May Reduce Efficacy of SPORANOX®
Antibacterials
Isoniazid Rifampicin | Not recommended 2 weeks before and during SPORANOX®treatment.
Rifabutin | Not recommended 2 weeks before, during, and 2 weeks after SPORANOX®treatment. See also Table 1.
Anticonvulsants
Phenobarbital Phenytoin | Not recommended 2 weeks before and during SPORANOX®treatment.
Carbamazepine | Not recommended 2 weeks before, during, and 2 weeks after SPORANOX®treatment. See also Table 1.
Antivirals
Efavirenz Nevirapine | Not recommended 2 weeks before and during SPORANOX®treatment.
Gastrointestinal Drugs
Drugs that reduce gastric acidity e.g. acid neutralizing medicines such as aluminum hydroxide, or acid secretion suppressors such as H2- receptor antagonists and proton pump inhibitors. | Use with caution. Administer acid neutralizing medicines at least 2 hours before or 2 hours after the intake of SPORANOX®capsules.
Miscellaneous Drugs and Other Substances
Lumacaftor/Ivacaftor | Not recommended 2 weeks before, during, and 2 weeks after SPORANOX®treatment.

Pediatric Population

Interaction studies have only been performed in adults.

Carcinogenesis, Mutagenesis, and Impairment of Fertility

Itraconazole showed no evidence of carcinogenicity potential in mice treated orally for 23 months at dosage levels up to 80 mg/kg/day (approximately 1 time the maximum recommended human dose [MRHD] of 400 mg/day based on body surface area comparisons). Male rats treated with 25 mg/kg/day (0.6 times the MRHD based on body surface area comparisons) had a slightly increased incidence of soft tissue sarcoma. These sarcomas may have been a consequence of hypercholesterolemia, which is a response of rats, but not dogs or humans, to chronic itraconazole administration. Female rats treated with 50 mg/kg/day (1.2 times the MRHD based on body surface area comparisons) had an increased incidence of squamous cell carcinoma of the lung (2/50) as compared to the untreated group. Although the occurrence of squamous cell carcinoma in the lung is extremely uncommon in untreated rats, the increase in this study was not statistically significant.

Itraconazole produced no mutagenic effects when assayed in DNA repair test (unscheduled DNA synthesis) in primary rat hepatocytes, in Ames tests with Salmonella typhimurium(6 strains) and Escherichia coli, in the mouse lymphoma gene mutation tests, in a sex-linked recessive lethal mutation (Drosophila melanogaster) test, in chromosome aberration tests in human lymphocytes, in a cell transformation test with C3H/10T½ C18 mouse embryo fibroblasts cells, in a dominant lethal mutation test in male and female mice, and in micronucleus tests in mice and rats.

Itraconazole did not affect the fertility of male or female rats treated orally with dosage levels of up to 40 mg/kg/day (1 time the MRHD based on body surface area comparisons), even though parental toxicity was present at this dosage level. More severe signs of parental toxicity, including death, were present in the next higher dosage level, 160 mg/kg/day (4 times the MRHD based on body surface area comparisons).

Pregnancy

Teratogenic Effects

Itraconazole was found to cause a dose-related increase in maternal toxicity, embryotoxicity, and teratogenicity in rats at dosage levels of approximately 40–160 mg/kg/day (1-4 times the MRHD based on body surface area comparisons), and in mice at dosage levels of approximately 80 mg/kg/day (1 time the MRHD based on body surface area comparisons). Itraconazole has been shown to cross the placenta in a rat model. In rats, the teratogenicity consisted of major skeletal defects; in mice, it consisted of encephaloceles and/or macroglossia.

There are no studies in pregnant women. SPORANOX®should be used for the treatment of systemic fungal infections in pregnancy only if the benefit outweighs the potential risk.

SPORANOX®should not be administered for the treatment of onychomycosis to pregnant patients or to women contemplating pregnancy. SPORANOX®should not be administered to women of childbearing potential for the treatment of onychomycosis unless they are using effective measures to prevent pregnancy and they begin therapy on the second or third day following the onset of menses. Highly effective contraception should be continued throughout SPORANOX®therapy and for 2 months following the end of treatment.

During postmarketing experience, cases of congenital abnormalities have been reported. (See ADVERSE REACTIONS: Postmarketing Experience.)

Nursing Mothers

Itraconazole is excreted in human milk; therefore, the expected benefits of SPORANOX®therapy for the mother should be weighed against the potential risk from exposure of itraconazole to the infant. The U.S. Public Health Service Centers for Disease Control and Prevention advises HIV-infected women not to breast-feed to avoid potential transmission of HIV to uninfected infants.

Pediatric Use

The efficacy and safety of SPORANOX®have not been established in pediatric patients.

The long-term effects of itraconazole on bone growth in children are unknown. In three toxicology studies using rats, itraconazole induced bone defects at dosage levels as low as 20 mg/kg/day (0.5 times the MRHD of 400 mg based on body surface area comparisons). The induced defects included reduced bone plate activity, thinning of the zona compacta of the large bones, and increased bone fragility. At a dosage level of 80 mg/kg/day (2 times the MRHD based on body surface area comparisons) over 1 year or 160 mg/kg/day (4 times the MRHD based on body surface area comparisons) for 6 months, itraconazole induced small tooth pulp with hypocellular appearance in some rats.

Geriatric Use

Clinical studies of SPORANOX® Capsules did not include sufficient numbers of subjects aged 65 years and over to determine whether they respond differently from younger subjects. It is advised to use SPORANOX® Capsules in these patients only if it is determined that the potential benefit outweighs the potential risks. In general, it is recommended that the dose selection for an elderly patient should be taken into consideration, reflecting the greater frequency of decreased hepatic, renal, or cardiac function, and of concomitant disease or other drug therapy.

Transient or permanent hearing loss has been reported in elderly patients receiving treatment with itraconazole. Several of these reports included concurrent administration of quinidine which is contraindicated (See BOXED WARNING: Drug Interactions, CONTRAINDICATIONS: Drug Interactions and PRECAUTIONS: Drug Interactions).

HIV-Infected Patients

Because hypochlorhydria has been reported in HIV-infected individuals, the absorption of itraconazole in these patients may be decreased.

Renal Impairment

Limited data are available on the use of oral itraconazole in patients with renal impairment. The exposure of itraconazole may be lower in some patients with renal impairment. Caution should be exercised when itraconazole is administered in this patient population and dose adjustment may be needed. (See CLINICAL PHARMACOLOGY: Special Populations and DOSAGE AND ADMINISTRATION.)

Hepatic Impairment

Limited data are available on the use of oral itraconazole in patients with hepatic impairment. Caution should be exercised when this drug is administered in this patient population. It is recommended that patients with impaired hepatic function be carefully monitored when taking SPORANOX®. It is recommended that the prolonged elimination half-life of itraconazole observed in the single oral dose clinical trial with itraconazole capsules in cirrhotic patients be considered when deciding to initiate therapy with other medications metabolized by CYP3A4.

In patients with elevated or abnormal liver enzymes or active liver disease, or who have experienced liver toxicity with other drugs, treatment with SPORANOX® is strongly discouraged unless there is a serious or life-threatening situation where the expected benefit exceeds the risk. It is recommended that liver function monitoring be done in patients with pre-existing hepatic function abnormalities or those who have experienced liver toxicity with other medications. (See CLINICAL PHARMACOLOGY: Special Populations and DOSAGE AND ADMINISTRATION.)

ADVERSE REACTIONS

Because clinical trials are conducted under widely varying conditions, adverse reaction rates observed in the clinical trials of a drug cannot be directly compared to rates in the clinical trials of another drug and may not reflect the rates observed in clinical practice.

SPORANOX® has been associated with rare cases of serious hepatotoxicity, including liver failure and death. Some of these cases had neither pre-existing liver disease nor a serious underlying medical condition. If clinical signs or symptoms develop that are consistent with liver disease, treatment should be discontinued and liver function testing performed. The risks and benefits of SPORANOX® use should be reassessed. (See WARNINGS: Hepatic Effects and PRECAUTIONS: Hepatotoxicity and Information for Patients.)

Adverse Events in the Treatment of Systemic Fungal Infections

Adverse event data were derived from 602 patients treated for systemic fungal disease in U.S. clinical trials who were immunocompromised or receiving multiple concomitant medications. Treatment was discontinued in 10.5% of patients due to adverse events. The median duration before discontinuation of therapy was 81 days (range: 2 to 776 days). The table lists adverse events reported by at least 1% of patients.

Table 3: Clinical Trials of Systemic Fungal Infections: Adverse Events Occurring with an Incidence of Greater than or Equal to 1%
Body System/Adverse Event | Incidence (%) (N=602)
Gastrointestinal
Nausea | 11
Vomiting | 5
Diarrhea | 3
Abdominal Pain | 2
Anorexia | 1
Body as a Whole
Edema | 4
Fatigue | 3
Fever | 3
Malaise | 1
Skin and Appendages
Rash [Rash tends to occur more frequently in immunocompromised patients receiving immunosuppressive medications.] | 9
Pruritus | 3
Central/Peripheral Nervous System
Headache | 4
Dizziness | 2
Psychiatric
Libido Decreased | 1
Somnolence | 1
Cardiovascular
Hypertension | 3
Metabolic/Nutritional
Hypokalemia | 2
Urinary System
Albuminuria | 1
Liver and Biliary System
Hepatic Function Abnormal | 3
Reproductive System, Male
Impotence | 1

Adverse events infrequently reported in all studies included constipation, gastritis, depression, insomnia, tinnitus, menstrual disorder, adrenal insufficiency, gynecomastia, and male breast pain.

Adverse Events Reported in Toenail Onychomycosis Clinical Trials

Patients in these trials were on a continuous dosing regimen of 200 mg once daily for 12 consecutive weeks.

The following adverse events led to temporary or permanent discontinuation of therapy.

Table 4: Clinical Trials of Onychomycosis of the Toenail: Adverse Events Leading to Temporary or Permanent Discontinuation of Therapy
Adverse Event | Incidence (%) Itraconazole (N=112)
Elevated Liver Enzymes (greater than twice the upper limit of normal) | 4
Gastrointestinal Disorders | 4
Rash | 3
Hypertension | 2
Orthostatic Hypotension | 1
Headache | 1
Malaise | 1
Myalgia | 1
Vasculitis | 1
Vertigo | 1

The following adverse events occurred with an incidence of greater than or equal to 1% (N=112): headache: 10%; rhinitis: 9%; upper respiratory tract infection: 8%; sinusitis, injury: 7%; diarrhea, dyspepsia, flatulence, abdominal pain, dizziness, rash: 4%; cystitis, urinary tract infection, liver function abnormality, myalgia, nausea: 3%; appetite increased, constipation, gastritis, gastroenteritis, pharyngitis, asthenia, fever, pain, tremor, herpes zoster, abnormal dreaming: 2%.

Adverse Events Reported in Fingernail Onychomycosis Clinical Trials

Patients in these trials were on a pulse regimen consisting of two 1-week treatment periods of 200 mg twice daily, separated by a 3-week period without drug.

The following adverse events led to temporary or permanent discontinuation of therapy.

Table 5: Clinical Trials of Onychomycosis of the Fingernail: Adverse Events Leading to Temporary or Permanent Discontinuation of Therapy
Adverse Event | Incidence (%) Itraconazole (N=37)
Rash/Pruritus | 3
Hypertriglyceridemia | 3

The following adverse events occurred with an incidence of greater than or equal to 1% (N=37): headache: 8%; pruritus, nausea, rhinitis: 5%; rash, bursitis, anxiety, depression, constipation, abdominal pain, dyspepsia, ulcerative stomatitis, gingivitis, hypertriglyceridemia, sinusitis, fatigue, malaise, pain, injury: 3%.

Adverse Events Reported from Other Clinical Trials

In addition, the following adverse drug reaction was reported in patients who participated in SPORANOX® Capsules clinical trials: Hepatobiliary Disorders:hyperbilirubinemia.

The following is a list of additional adverse drug reactions associated with itraconazole that have been reported in clinical trials of SPORANOX® Oral Solution and itraconazole IV excluding the adverse reaction term "Injection site inflammation" which is specific to the injection route of administration:

Cardiac Disorders: cardiac failure, left ventricular failure, tachycardia;

General Disorders and Administration Site Conditions: face edema, chest pain, chills;

Hepatobiliary Disorders: hepatic failure, jaundice;

Investigations:alanine aminotransferase increased, aspartate aminotransferase increased, blood alkaline phosphatase increased, blood lactate dehydrogenase increased, blood urea increased, gamma-glutamyltransferase increased, urine analysis abnormal;

Metabolism and Nutrition Disorders: hyperglycemia, hyperkalemia, hypomagnesemia;

Psychiatric Disorders: confusional state;

Renal and Urinary Disorders: renal impairment;

Respiratory, Thoracic and Mediastinal Disorders: dysphonia, cough;

Skin and Subcutaneous Tissue Disorders: rash erythematous, hyperhidrosis;

Vascular Disorders: hypotension

Postmarketing Experience

Adverse drug reactions that have been first identified during postmarketing experience with SPORANOX®(all formulations) are listed in the table below. Because these reactions are reported voluntarily from a population of uncertain size, reliably estimating their frequency or establishing a causal relationship to drug exposure is not always possible.

Table 6: Postmarketing Reports of Adverse Drug Reactions
Blood and Lymphatic System Disorders: | Leukopenia, neutropenia, thrombocytopenia
Immune System Disorders: | Anaphylaxis; anaphylactic, anaphylactoid and allergic reactions; serum sickness; angioneurotic edema
Endocrine Disorders: | Pseudoaldosteronism
Nervous System Disorders: | Peripheral neuropathy, paresthesia, hypoesthesia, tremor
Eye Disorders: | Visual disturbances, including vision blurred and diplopia
Ear and Labyrinth Disorders: | Transient or permanent hearing loss
Cardiac Disorders: | Congestive heart failure, bradycardia
Respiratory, Thoracic and Mediastinal Disorders: | Pulmonary edema, dyspnea
Gastrointestinal Disorders: | Pancreatitis, dysgeusia
Hepatobiliary Disorders: | Serious hepatotoxicity (including some cases of fatal acute liver failure), hepatitis
Skin and Subcutaneous Tissue Disorders: | Toxic epidermal necrolysis, Stevens-Johnson syndrome, acute generalized exanthematous pustulosis, erythema multiforme, exfoliative dermatitis, leukocytoclastic vasculitis, alopecia, photosensitivity, urticaria
Musculoskeletal and Connective Tissue Disorders: | Arthralgia
Renal and Urinary Disorders: | Urinary incontinence, pollakiuria
Reproductive System and Breast Disorders: | Erectile dysfunction
General Disorders and Administration Site Conditions: | Peripheral edema
Investigations: | Blood creatine phosphokinase increased

There is limited information on the use of SPORANOX®during pregnancy. Cases of congenital abnormalities including skeletal, genitourinary tract, cardiovascular and ophthalmic malformations as well as chromosomal and multiple malformations have been reported during postmarketing experience. A causal relationship with SPORANOX®has not been established. (See CLINICAL PHARMACOLOGY: Special Populations, CONTRAINDICATIONS, WARNINGS, and PRECAUTIONS: Drug Interactions for more information.)

OVERDOSAGE

Itraconazole is not removed by dialysis. In the event of accidental overdosage, supportive measures should be employed. Contact a certified poison control center for the most up to date information on the management of SPORANOX®Capsules overdosage (1-800-222-1222 or www.poison.org).

In general, adverse events reported with overdose have been consistent with adverse drug reactions already listed in this package insert for itraconazole. (See ADVERSE REACTIONS.)

DOSAGE AND ADMINISTRATION

SPORANOX®(itraconazole) Capsules should be taken with a full meal to ensure maximal absorption. SPORANOX®(itraconazole) Capsules must be swallowed whole.

SPORANOX®Capsules is a different preparation than SPORANOX®Oral Solution and should not be used interchangeably.

Treatment of Blastomycosis and Histoplasmosis

The recommended dose is 200 mg once daily (2 capsules). If there is no obvious improvement, or there is evidence of progressive fungal disease, the dose should be increased in 100-mg increments to a maximum of 400 mg daily. Doses above 200 mg/day should be given in two divided doses.

Treatment of Aspergillosis

A daily dose of 200 to 400 mg is recommended.

Treatment in Life-Threatening Situations

In life-threatening situations, a loading dose should be used.

Although clinical studies did not provide for a loading dose, it is recommended, based on pharmacokinetic data, that a loading dose of 200 mg (2 capsules) three times daily (600 mg/day) be given for the first 3 days of treatment.

Treatment should be continued for a minimum of three months and until clinical parameters and laboratory tests indicate that the active fungal infection has subsided. An inadequate period of treatment may lead to recurrence of active infection.

SPORANOX®Capsules and SPORANOX®Oral Solution should not be used interchangeably. Only the oral solution has been demonstrated effective for oral and/or esophageal candidiasis.

Treatment of Onychomycosis

Toenails with or without fingernail involvement

The recommended dose is 200 mg (2 capsules) once daily for 12 consecutive weeks.

Treatment of Onychomycosis

Fingernails only

The recommended dosing regimen is 2 treatment pulses, each consisting of 200 mg (2 capsules) b.i.d. (400 mg/day) for 1 week. The pulses are separated by a 3-week period without SPORANOX®.

Use in Patients with Renal Impairment

Limited data are available on the use of oral itraconazole in patients with renal impairment. Caution should be exercised when this drug is administered in this patient population. (See CLINICAL PHARMACOLOGY: Special Populations and PRECAUTIONS.)

Use in Patients with Hepatic Impairment

Limited data are available on the use of oral itraconazole in patients with hepatic impairment. Caution should be exercised when this drug is administered in this patient population. (See CLINICAL PHARMACOLOGY: Special Populations, WARNINGS, and PRECAUTIONS.)

HOW SUPPLIED

SPORANOX®(itraconazole) Capsules are available containing 100 mg of itraconazole, with a blue opaque cap and pink transparent body, imprinted with "JANSSEN" and "SPORANOX 100." The capsules are supplied in unit-dose blister packs of 3 × 10 capsules (NDC 50458-290-01) and bottles of 30 capsules (NDC 50458-290-04).

STORAGE AND HANDLING

Store at controlled room temperature 15°–25°C (59°–77°F). Protect from light and moisture.

For patent information: www.janssenpatents.com

PATIENT INFORMATION
SPORANOX®(SPOR-ah-nox)
(itraconazole)
Capsules

Read this Patient Information that comes with SPORANOX before you start taking it and each time you get a refill. There may be new information. This information does not take the place of talking with your healthcare provider about your medical condition or your treatment.

What is the most important information I should know about SPORANOX?
SPORANOX can cause serious side effects, including:

1. Heart failure. Do not take SPORANOX if you have had heart failure, including congestive heart failure.
  Stop taking SPORANOX and call your healthcare provider right away if you have any of these symptoms of congestive heart failure:

- shortness of breath
- swelling of your feet, ankles or legs
- sudden weight gain
- increased tiredness

- coughing up white or pink mucus (phlegm)
- fast heartbeat
- waking up at night more than normal for you

1. Heart problems and other serious medical problems. Serious medical problems that affect the heart and other parts of your body can happen if you take SPORANOX with certain other medicines. Do not take SPORANOX if you also take the following medicines:

- methadone
- disopyramide
- dofetilide
- dronedarone
- quinidine
- isavuconazole
- ergot alkaloids (such as dihydroergotamine, ergometrine ergonovine)
- ergotamine
- methylergometrine (methylergonovine)

- irinotecan
- lurasidone
- oral midazolam
- pimozide
- triazolam
- felodipine
- nisoldipine
- ivabradine
- ranolazine
- eplerenone
- cisapride

- naloxegol
- lomitapide
- lovastatin
- simvastatin
- avanafil
- ticagrelor
- venetoclax (see below)
- finerenone
- voclosporin

Do nottake SPORANOX with venetoclax for chronic lymphocytic leukemia/small lymphocytic lymphoma when you first start treatment with venetoclax or with increasing doses of venetoclax.
This is not a complete list of medicines that can interact with SPORANOX. SPORANOX may affect the way other medicines work, and other medicines may affect how SPORANOX works. You can ask your pharmacist for a list of medicines that interact with SPORANOX.
Before you start taking SPORANOX, tell your healthcare provider about all the medicines you take, including prescription and over-the-counter medicines, vitamins, and herbal supplements. Before you start any new medicine, ask your healthcare provider or pharmacist if it is safe to take it with SPORANOX.

1. Liver problems. SPORANOX can cause serious liver problems which may be severe and lead to death. Stop taking SPORANOX and call your healthcare provider right away if you have any of these symptoms of liver problems:

- tiredness
- loss of appetite for several days or longer
- nausea or vomiting
- dark or "tea-colored" urine

- your skin or the white part of your eyes turn yellow (jaundice)
- light-colored stools (bowel movement)

For more information about side effects, see " What are the possible side effects of SPORANOX?"

What is SPORANOX?

- SPORANOX is a prescription medicine used to treat the following fungal infections of the toenails, fingernails and other parts of the body: blastomycosis, histoplasmosis, aspergillosis, and onychomycosis.
- It is not known if SPORANOX is safe and effective in children.

Do not take SPORANOX if you:

- have or have had heart failure, including congestive heart failure.
- take certain medicines. See " What is the most important information I should know about SPORANOX?"
- are pregnant or plan to become pregnant. SPORANOX can harm your unborn baby. Tell your healthcare provider right away if you become pregnant while taking SPORANOX. Females who are able to become pregnant must use effective forms of birth control during treatment and for 2 months after stopping treatment with SPORANOX.
- are allergic to itraconazole or any of the ingredients in SPORANOX. See the end of this Patient Information leaflet for a complete list of ingredients in SPORANOX.

Before taking SPORANOX, tell your healthcare provider about all of your medical conditions, including if you:

- have heart problems.
- have liver problems.
- have kidney problems.
- have a weakened immune system (immunocompromised).
- have lung problems including cystic fibrosis.
- are breastfeeding or plan to breastfeed. SPORANOX can pass into your breast milk. You and your healthcare provider should decide if you will take SPORANOX or breastfeed.

Taking SPORANOX with certain medicines may affect each other. Taking SPORANOX with other medicines can cause serious side effects.

How should I take SPORANOX?

- Take SPORANOX exactly as prescribed by your healthcare provider. Your healthcare provider will tell you how much SPORANOX to take and when to take it.
- You will receive SPORANOX capsules in a blister pack or bottle. Your healthcare provider will decide the type of SPORANOX that is right for you.
- Take SPORANOX with a full meal.
- Swallow SPORANOX capsules whole.
- You should not take SPORANOX oral solution instead of SPORANOX capsules, because they will not work the same way.
- If you take too much SPORANOX, call your healthcare provider or go to the nearest hospital emergency room right away.

What should I avoid while taking SPORANOX?
SPORANOX can cause dizziness and vision problems. Do not drive or operate machinery until you know how SPORANOX affects you.

What are the possible side effects of SPORANOX?
SPORANOX may cause serious side effects, including:

- See What is the most important information I should know about SPORANOX?"
- New or worsening high blood pressure and low potassium levels in your blood (pseudoaldosteronism).Your healthcare provider should check your blood pressure and potassium levels.
- Nerve problems (neuropathy).Call your healthcare provider right away if you have tingling or numbness in your hands or feet. Your healthcare provider may stop your treatment with SPORANOX if you have nerve problems.
- Hearing loss.Hearing loss can happen for a short time or permanently in some people who take SPORANOX. Stop taking SPORANOX and call your healthcare provider right away if you have any changes in your hearing.

The most common side effects of SPORANOX include: headache, rash, digestive system problems (such as nausea and vomiting), and edema.
Additional possible side effects include upset stomach, constipation, fever, inflammation of the pancreas, increase in blood pressure, menstrual disorder, erectile dysfunction, dizziness, muscle pain, painful joints, unpleasant taste, or hair loss.
These are not all the possible side effects of SPORANOX.
Call your doctor for medical advice about side effects. You may report side effects to FDA at 1-800-FDA-1088.

How should I store SPORANOX?

- Store SPORANOX at room temperature between 59°F to 77°F (15°C to 25°C).
- Keep SPORANOX dry and away from light.

Keep SPORANOX and all medicines out of the reach of children.

General information about the safe and effective use of SPORANOX.
Medicines are sometimes prescribed for purposes other than those listed in a Patient Information leaflet. Do not use SPORANOX for a condition for which it was not prescribed. Do not give SPORANOX to other people, even if they have the same symptoms that you have. It may harm them.
You can ask your doctor or pharmacist for information about SPORANOX that is written for health professionals.

What are the ingredients in SPORANOX?
Active ingredients : itraconazole
Inactive ingredients: hard gelatin capsule, hypromellose, polyethylene glycol (PEG) 20,000, titanium dioxide, FD&C Blue No. 1, FD&C Blue No. 2, D&C Red No. 22 and D&C Red No. 28.
Manufactured for: Janssen Pharmaceuticals, Inc. Titusville, NJ 08560, USA
For patent information: www.janssenpatents.com
© 2024 Janssen Pharmaceutical Companies
For more information or call 1-800-526-7736.

This Patient Information has been approved by the U.S. Food and Drug Administration

Revised: 10/2024

© 2024 Janssen Pharmaceutical Companies

Revised: 12/2024

Manufactured for:

Janssen Pharmaceuticals, Inc.

Titusville, NJ 08560, USA

PRINCIPAL DISPLAY PANEL - 100 mg Capsule Bottle Label

30 Capsules
NDC 50458-290-04

100 mg
sporanox®
(itraconazole)
Capsules

Each capsule contains:
itraconazole 100 mg

janssen

Rx only